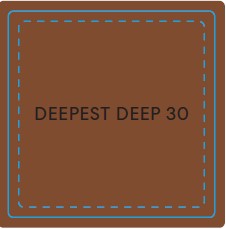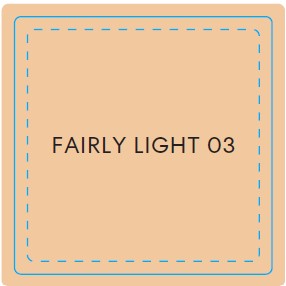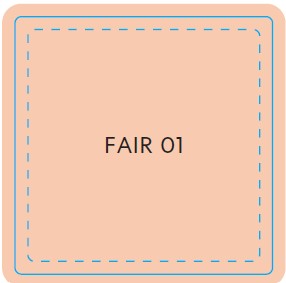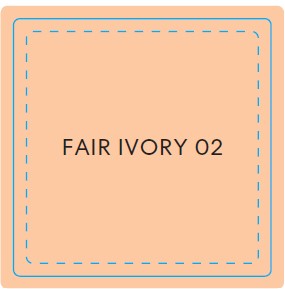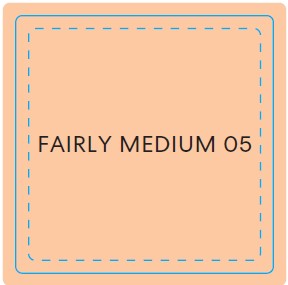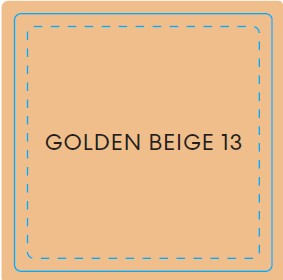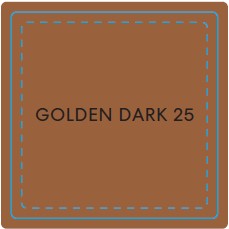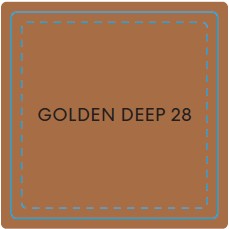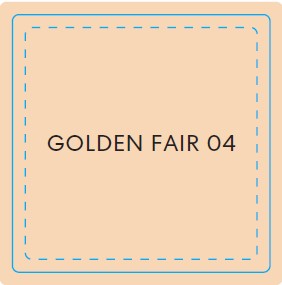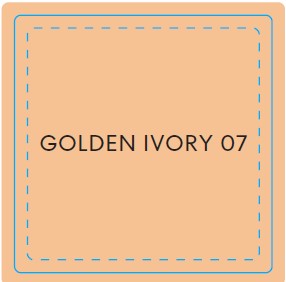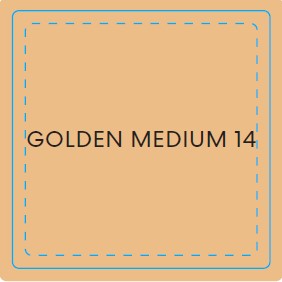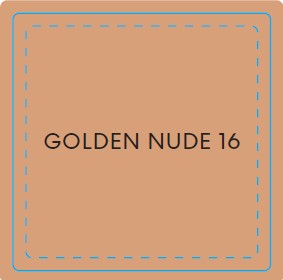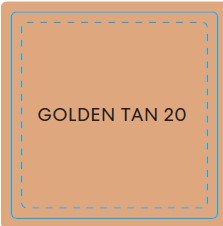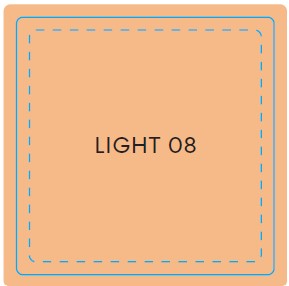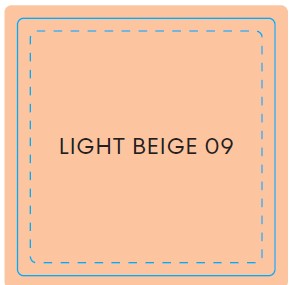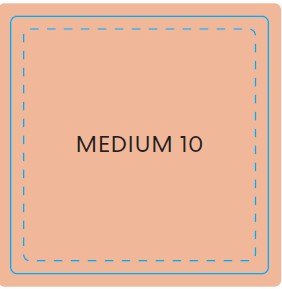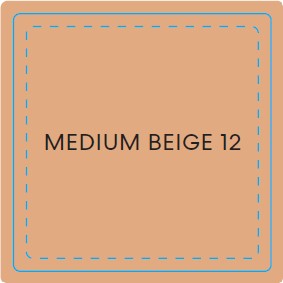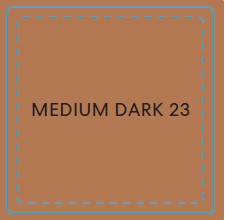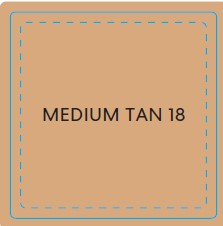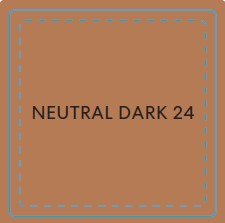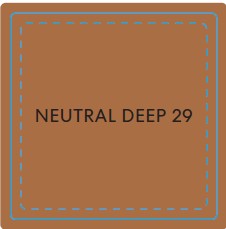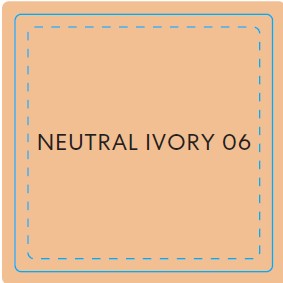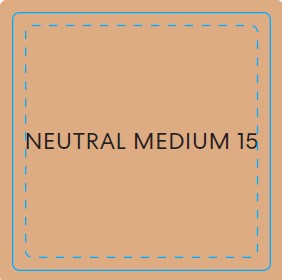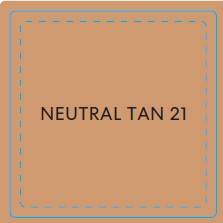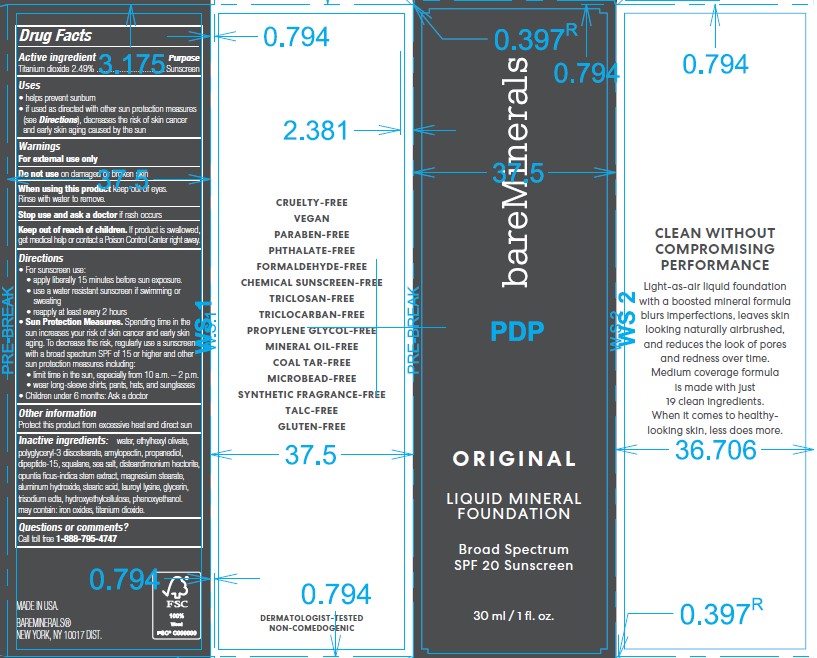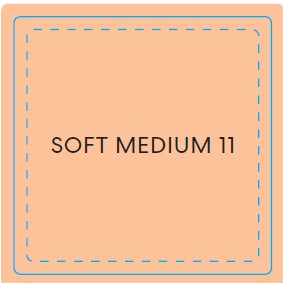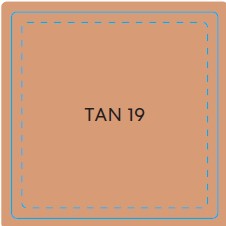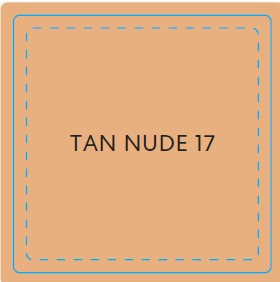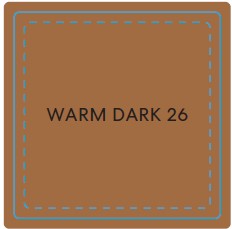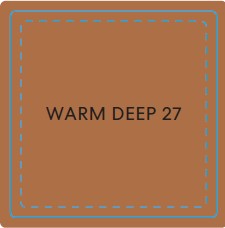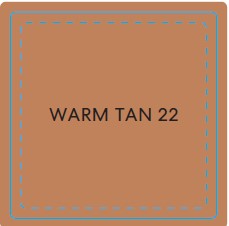 DRUG LABEL: bareMinerals ORIGINAL Liquid Mineral Foundation Broad Spectrum SPF 20 Sunscreen
NDC: 98132-041 | Form: LIQUID
Manufacturer: Orveon Global US, LLC
Category: otc | Type: HUMAN OTC DRUG LABEL
Date: 20231004

ACTIVE INGREDIENTS: TITANIUM DIOXIDE 0.747 mg/1 mL
INACTIVE INGREDIENTS: POLYGLYCERYL-3 DIISOSTEARATE; MAGNESIUM STEARATE; STEARIC ACID; PHENOXYETHANOL; ETHYLHEXYL OLEATE; SQUALANE; OPUNTIA FICUS-INDICA STEM; ALUMINUM HYDROXIDE; LAUROYL LYSINE; GLYCERIN; EDETATE TRISODIUM; HYDROXYETHYL CELLULOSE, UNSPECIFIED; WATER; PROPANEDIOL; DIGLYCINE; DISTEARDIMONIUM HECTORITE; SEA SALT; FERRIC OXIDE RED; AMYLOPECTIN (4,5-DIHYDROXY-1,3-DIMETHYLIMIDAZOLIDIN-2-ONE CROSS LINKED)

bareMinerals ORIGINAL Liquid Mineral Foundation Broad Spectrum SPF 20 Sunscreen

Purpose

Active Ingredient Purpose

Titanium Dioxide 2.49% Sunscreen

Uses

Helps prevent sunburn.

If used as directed with other sun protection measures (see Directions), decreases the risk of skin cancer and early skin aging caused by the sun

Warnings

For external use only

Do not use

- on damaged or broken skin.

When using this product

- keep out of eyes. Rinse with water to remove.

Stop use and ask a doctor if

- rash occurs.

Keep out of reach of children.

If swallowed, get medical help or contact a Poison Control Center right away.

Directions

- apply liberally 15 minutes before sun exposure
- reapply at least every 2 hours
- use a water resistant sunscreen if swimming or sweating
- Sun Protection Measures. Spending time in the sun increases your risk of skin cancer and early skin aging. To decrease this risk, regularly use a sunscreen with a Broad Spectrum SPF value of 15 or higher and other sun protection measures including:
- limit time in the sun, especially from 10 a.m.-2 p.m.
- wear long-sleeved shirts, pants, hats, and sunglasses
- children under 6 months of age: Ask a doctor

Inactive ingredients

water, ethylhexyl olivate, polyglyceryl-3 diisostearate, amylopectin, propanediol, dipeptide-15, squalane, sea salt, disteardimonium hectorite, opuntia ficus-indica stem extract, magnesium stearate, aluminum hydroxide, stearic acid, lauroyl lysine, glycerin, trisodium edta, hydroxyethylcellulose, phenoxyethanol. may contain: iron oxides, titanium dioxide.

OTHER SAFETY INFORMATION

Protect this product from excessive heat and direct sun.

Principal Display Panel - 30 mL / 1 fl. oz. - FAIR 01

bareMinerals

ORIGINAL

Liquid Mineral Foundation

Broad Spectrum SPF 20 Sunscreen

30 mL / 1 fl. oz.

Principal Display Panel - 30 mL / 1 fl. oz. - FAIR IVORY 02

bareMinerals
ORIGINAL
Liquid Mineral Foundation
Broad Spectrum SPF 20 Sunscreen
30 mL / 1 fl. oz.

Principal Display Panel - 30 mL / 1 fl. oz - FAIRLY LIGHT 03

bareMinerals
ORIGINAL
Liquid Mineral Foundation
Broad Spectrum SPF 20 Sunscreen
30 mL / 1 fl. oz.

Principal Display Panel - 30 mL / 1 fl. oz. - GOLDEN FAIR 04

bareMinerals
ORIGINAL
Liquid Mineral Foundation
Broad Spectrum SPF 20 Sunscreen
30 mL / 1 fl. oz.

Principal Display Panel - 30 mL / 1 fl. oz. - FAIRLY MEDIUM 05

bareMinerals
ORIGINAL
Liquid Mineral Foundation
Broad Spectrum SPF 20 Sunscreen
30 mL / 1 fl. oz.

Principal Display Panel - 30 mL / 1 fl. oz. - SOFT MEDIUM 11

bareMinerals
ORIGINAL
Liquid Mineral Foundation
Broad Spectrum SPF 20 Sunscreen
30 mL / 1 fl. oz.

Principal Display Panel - 30 mL / 1 fl. oz. - NEUTRAL IVORY 06

bareMinerals
ORIGINAL
Liquid Mineral Foundation
Broad Spectrum SPF 20 Sunscreen
30 mL / 1 fl. oz.

Principal Display Panel - 30 mL / 1 fl. oz. - LIGHT 08

bareMinerals
ORIGINAL
Liquid Mineral Foundation
Broad Spectrum SPF 20 Sunscreen
30 mL / 1 fl. oz.

Principal Display Panel - 30 mL / 1 fl. oz. - GOLDEN IVORY 07

bareMinerals
ORIGINAL
Liquid Mineral Foundation
Broad Spectrum SPF 20 Sunscreen
30 mL / 1 fl. oz.

Principal Display Panel - 30 mL / 1 fl. oz. - LIGHT BEIGE 09

bareMinerals
ORIGINAL
Liquid Mineral Foundation
Broad Spectrum SPF 20 Sunscreen
30 mL / 1 fl. oz.

Principal Display Panel - 30 mL / 1 fl. oz. - MEDIUM BEIGE 12

bareMinerals
ORIGINAL
Liquid Mineral Foundation
Broad Spectrum SPF 20 Sunscreen
30 mL / 1 fl. oz.

Principal Display Panel - 30 mL / 1 fl. oz. - GOLDEN BEIGE 13

bareMinerals
ORIGINAL
Liquid Mineral Foundation
Broad Spectrum SPF 20 Sunscreen
30 mL / 1 fl. oz.

Principal Display Panel - 30 mL / 1 fl. oz. - GOLDEN MEDIUM 14

bareMinerals
ORIGINAL
Liquid Mineral Foundation
Broad Spectrum SPF 20 Sunscreen
30 mL / 1 fl. oz.

Principal Display Panel - 30 mL / 1 fl. oz. - MEDIUM 10

bareMinerals
ORIGINAL
Liquid Mineral Foundation
Broad Spectrum SPF 20 Sunscreen
30 mL / 1 fl. oz.

Principal Display Panel - 30 mL / 1 fl. oz. - NEUTRAL MEDIUM 15

bareMinerals
ORIGINAL
Liquid Mineral Foundation
Broad Spectrum SPF 20 Sunscreen
30 mL / 1 fl. oz.

Principal Display Panel - 30 mL / 1 fl. oz. - GOLDEN TAN 20

bareMinerals
ORIGINAL
Liquid Mineral Foundation
Broad Spectrum SPF 20 Sunscreen
30 mL / 1 fl. oz.

Principal Display Panel - 30 mL / 1 fl. oz. - GOLDEN NUDE 16

bareMinerals
ORIGINAL
Liquid Mineral Foundation
Broad Spectrum SPF 20 Sunscreen
30 mL / 1 fl. oz.

Principal Display Panel - 30 mL / 1 fl. oz. - MEDIUM TAN 18

bareMinerals
ORIGINAL
Liquid Mineral Foundation
Broad Spectrum SPF 20 Sunscreen
30 mL / 1 fl. oz.

Principal Display Panel - 30 mL / 1 fl. oz. - TAN NUDE 17

bareMinerals
ORIGINAL
Liquid Mineral Foundation
Broad Spectrum SPF 20 Sunscreen
30 mL / 1 fl. oz.

Principal Display Panel - 30 mL / 1 fl. oz. - TAN 19

bareMinerals
ORIGINAL
Liquid Mineral Foundation
Broad Spectrum SPF 20 Sunscreen
30 mL / 1 fl. oz.

Principal Display Panel - 30 mL / 1 fl. oz. - NEUTRAL TAN 21

bareMinerals
ORIGINAL
Liquid Mineral Foundation
Broad Spectrum SPF 20 Sunscreen
30 mL / 1 fl. oz.

Principal Display Panel - 30 mL / 1 fl. oz. - WARM TAN 22

bareMinerals
ORIGINAL
Liquid Mineral Foundation
Broad Spectrum SPF 20 Sunscreen
30 mL / 1 fl. oz.

Principal Display Panel - 30 mL / 1 fl. oz. - NEUTRAL DARK 24

bareMinerals
ORIGINAL
Liquid Mineral Foundation
Broad Spectrum SPF 20 Sunscreen
30 mL / 1 fl. oz.

Principal Display Panel - 30 mL / 1 fl. oz. - GOLDEN DARK 25

bareMinerals
ORIGINAL
Liquid Mineral Foundation
Broad Spectrum SPF 20 Sunscreen
30 mL / 1 fl. oz.

Principal Display Panel - 30 mL / 1 fl. oz. - WARM DARK 26

bareMinerals
ORIGINAL
Liquid Mineral Foundation
Broad Spectrum SPF 20 Sunscreen
30 mL / 1 fl. oz.

Principal Display Panel - 30 mL / 1 fl. oz. - MEDIUM DARK 23

bareMinerals
ORIGINAL
Liquid Mineral Foundation
Broad Spectrum SPF 20 Sunscreen
30 mL / 1 fl. oz.

Principal Display Panel - 30 mL / 1 fl. oz. - WARM DEEP 27

bareMinerals
ORIGINAL
Liquid Mineral Foundation
Broad Spectrum SPF 20 Sunscreen
30 mL / 1 fl. oz.

Principal Display Panel - 30 mL / 1 fl. oz. - DEEPEST DEEP 30

bareMinerals
ORIGINAL
Liquid Mineral Foundation
Broad Spectrum SPF 20 Sunscreen
30 mL / 1 fl. oz.

Principal Display Panel - 30 mL / 1 fl. oz. - GOLDEN DEEP 28

bareMinerals
ORIGINAL
Liquid Mineral Foundation
Broad Spectrum SPF 20 Sunscreen
30 mL / 1 fl. oz.

Principal Display Panel - 30 mL / 1 fl. oz. - NEUTRAL DEEP 29

bareMinerals
ORIGINAL
Liquid Mineral Foundation
Broad Spectrum SPF 20 Sunscreen
30 mL / 1 fl. oz.